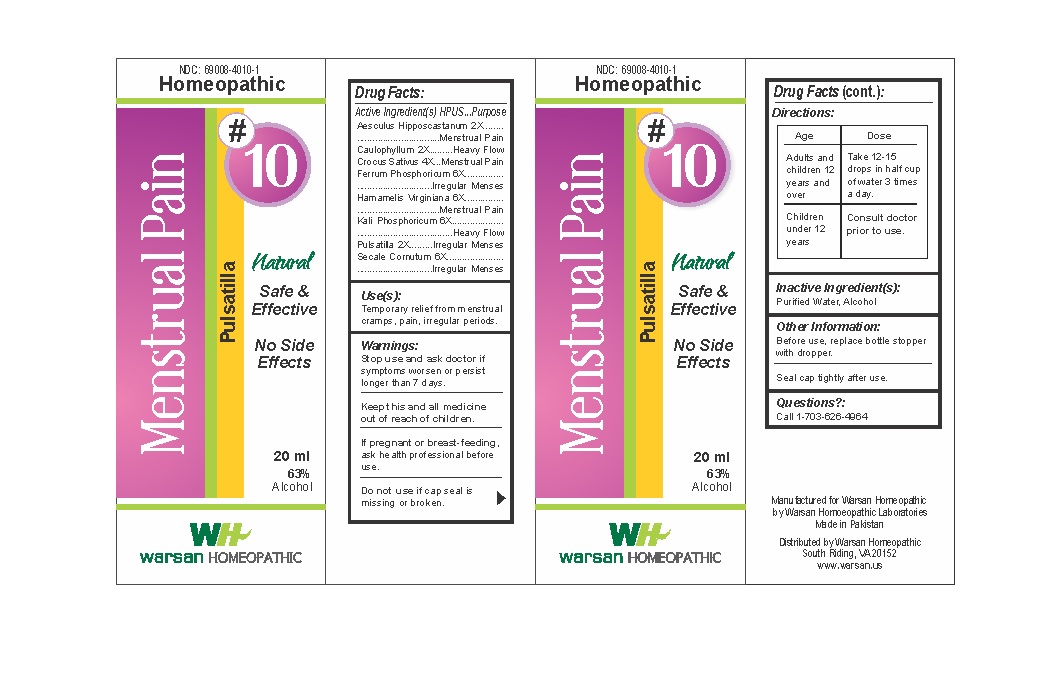 DRUG LABEL: Combination Remedy 10 - Menstrual Pain
NDC: 69008-4010 | Form: SOLUTION/ DROPS
Manufacturer: Warsan Homoeopathic Laboratories
Category: homeopathic | Type: HUMAN OTC DRUG LABEL
Date: 20171225

ACTIVE INGREDIENTS: SAFFRON 4 [hp_X]/1 mL; FERRUM PHOSPHORICUM 6 [hp_X]/1 mL; HORSE CHESTNUT 2 [hp_X]/1 mL; POTASSIUM PHOSPHATE, DIBASIC 6 [hp_X]/1 mL; CLAVICEPS PURPUREA SCLEROTIUM 6 [hp_X]/1 mL; PULSATILLA VULGARIS 2 [hp_X]/1 mL; CAULOPHYLLUM THALICTROIDES ROOT 2 [hp_X]/1 mL; HAMAMELIS VIRGINIANA ROOT BARK/STEM BARK 6 [hp_X]/1 mL
INACTIVE INGREDIENTS: ALCOHOL; WATER

Stop use and ask doctor if symptoms worsen or persist longer than 7 days.

If pregnant or breast-feeding, ask health professional before use.

Do not use if tamper evident seal is missing or broken.

Keep out of reach of children.

ACTIVE INGREDIENT

Aesculus Hipposcastanum 2X

Caulophyllum 2X

Crocus Sativus 4X

Ferrum Phosphoricum 6X

Hamamelis Virginiana 6X

Kali Phosphoricum 6X

Pulsatilla 2X

Secale Cornutum 6X

PURPOSE

Temporary relief from menstrual cramps, pain, irregular periods.

INACTIVE INGREDIENT

Purified Water

Alcohol

DOSAGE AND ADMINISTRATION

Adults and children 12 years and older: Take 10-15 drops in half cup of water 3 times a day.

Children under 12 years: Not intended for use by children under 12.

INDICATIONS AND USAGE

Temporary relief from menstrual cramps, pain, irregular periods.